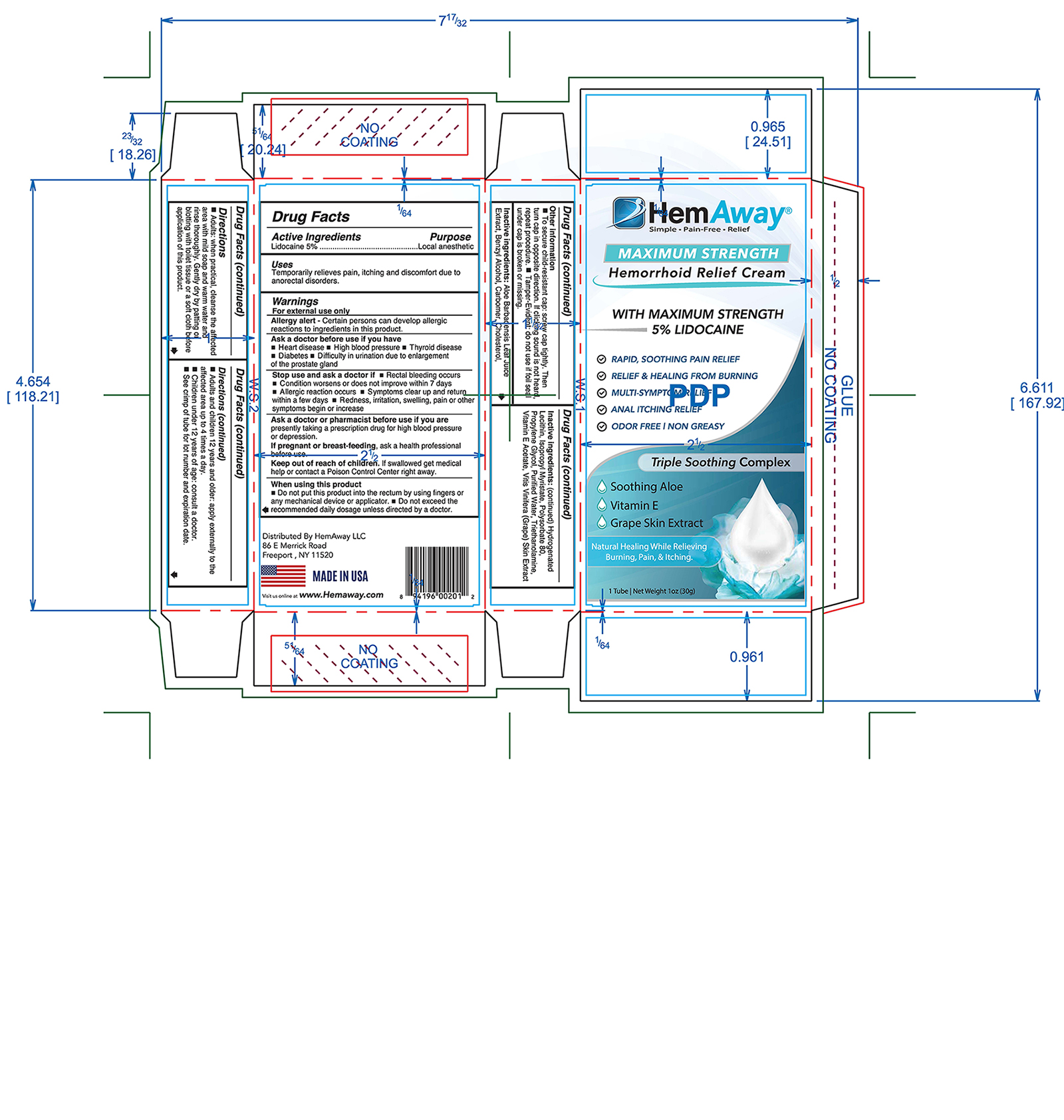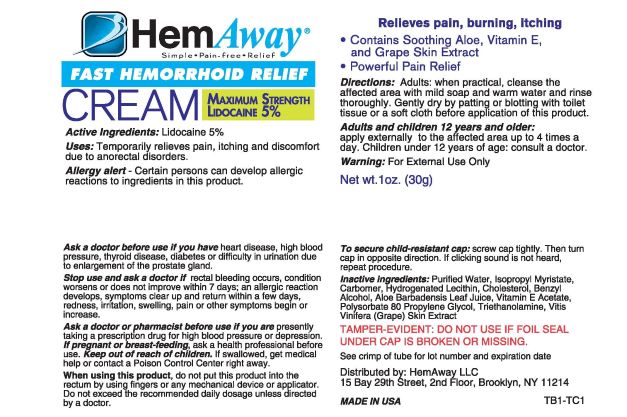 DRUG LABEL: HemAway
NDC: 54473-336 | Form: CREAM
Manufacturer: Melaleuca, Inc.
Category: otc | Type: HUMAN OTC DRUG LABEL
Date: 20250327

ACTIVE INGREDIENTS: LIDOCAINE 1.5 g/30 g
INACTIVE INGREDIENTS: BENZYL ALCOHOL; CARBOMER HOMOPOLYMER TYPE C; CHOLESTEROL; HYDROGENATED SOYBEAN LECITHIN; ISOPROPYL MYRISTATE; POLYSORBATE 80; PROPYLENE GLYCOL; WATER; TROLAMINE; ALPHA-TOCOPHEROL ACETATE; GRAPE; ALOE VERA LEAF

HemAway Maximum Strength Hemorrhoid Relief Cream

Uses

Temporarily relieves pain, itching and discomfort due to anorectal disorders.

Warnings

For External use only

Allergy alert: Certain persons can develop allergic reactions to ingredients in this product.

Directions

- Adults: when practical, cleanse the affected area with mild soap and warm water and rinse thoroughly. Gently dry by patting or blotting with toilet tissue or a soft cloth before application of this product.
- Adults and children 12 years and older: apply externally to the affected area up to 4 times a day.
- Children under 12 years of age: consult a doctor.

Other information

- To secure child-resistant cap: screw cap tightly. Then turn cap in opposite direction. If clicking sound is not heard, repeat procedure.
- Tamper-Evident: do not use if foil seal under cap is broken or missing.
- See crimp of tube for lot number and expiration date.

INACTIVE INGREDIENT

Inactive ingredients: Aloe Barbadensis Leaf Juice Extract, Benzyl Alcohol, Carbomer, Cholesterol, Hydrogenated Lecithin, Isopropyl Myristate, Polysorbate 80, Propylene Glycol, Purified Water, Triethanolamine, vitamin E Acetate, Vitis Vinifera (Grape) Skin Extract

Active Ingredients
Lidocaine 5%

PURPOSE

Local anesthetic

Keep out of reach of children. If swallowed get medical help or contact a Poison Control Center right away.

Ask a Doctor before use, if you have:

- Heart Disease
- High Blood Pressure
- Thyroid Disease
- Diabetes
- Difficulty in urination due to enlargement of the prostate gland

Stop use and ask a Doctor if:

- Rectal bleeding occurs
- Conditions worsens or does not improve within 7 days
- Allergic reaction occurs
- Symptoms clear up and return in a few days
- Redness, irritation, swelling, pain or other symptoms begin or increase

Ask a Doctor or Pharmacist if you are: Presently taking a prescription drug for high blood pressure or depression.

PREGNANCY OR BREAST FEEDING

If pregnant or breast feeding ask a health professional before use.

When using this product:

- Do not put this product into the rectum by using fingers or any mechanical device or applicator.
- Do not exceed the recommended daily dosage unless directed by a doctor.